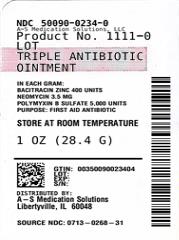 DRUG LABEL: Triple Antibiotic
NDC: 50090-0234 | Form: OINTMENT
Manufacturer: A-S Medication Solutions
Category: otc | Type: HUMAN OTC DRUG LABEL
Date: 20241106

ACTIVE INGREDIENTS: POLYMYXIN B SULFATE 5000 [USP'U]/1 g; NEOMYCIN SULFATE 3.5 mg/1 g; BACITRACIN ZINC 400 [USP'U]/1 g
INACTIVE INGREDIENTS: LIGHT MINERAL OIL; PETROLATUM

ACTIVE INGREDIENT (in each gram)

Bacitracin zinc 400 units
Neomycin 3.5 mg
Polymyxin B sulfate 5,000 units

PURPOSE

First aid antibiotic

USES

first aid to help prevent infection in minor
• cuts
• scrapes
• burns

WARNINGS

For external use only
Do not use
• if you are allergic to any of the ingredients
• in the eyes
• over large areas of the body
• longer than 1 week unless directed by a doctor
Ask a doctor before use if you have
• deep or puncture wounds
• animal bites
• serious burns
Stop use and ask a doctor if
• the condition persists or gets worse
• a rash or other allergic reaction develops

KEEP OUT OF REACH OF CHILDREN

If swallowed, get medical help or contact a Poison Control Center right away.

DIRECTIONS

• clean the affected area
• apply a small amount of this product (an amount equal to the surface area of the tip of a finger) on the area 1 to 3 times daily
• may be covered with a sterile bandage

OTHER INFORMATION

store at room temperature

INACTIVE INGREDIENT

light mineral oil, white petrolatum

HOW SUPPLIED

Product: 50090-0234

NDC: 50090-0234-0 28.4 g in a TUBE